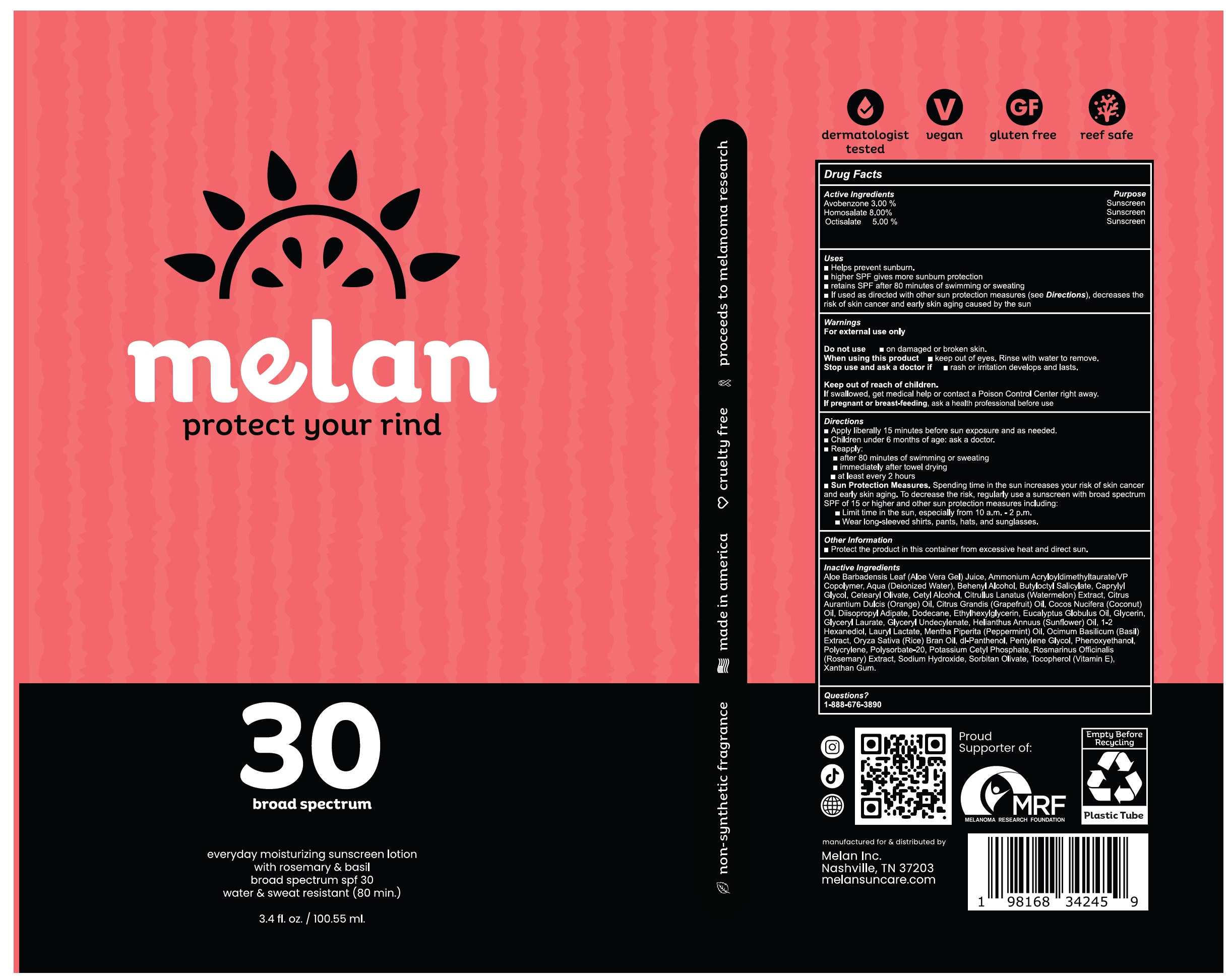 DRUG LABEL: MELAN SPF-30 Broad Spectrum
NDC: 84294-484 | Form: LOTION
Manufacturer: MELAN INC.
Category: otc | Type: HUMAN OTC DRUG LABEL
Date: 20240502

ACTIVE INGREDIENTS: AVOBENZONE 30 mg/1 mL; HOMOSALATE 80 mg/1 mL; OCTISALATE 50 mg/1 mL
INACTIVE INGREDIENTS: ALOE VERA LEAF; AMMONIUM ACRYLOYLDIMETHYLTAURATE/VP COPOLYMER; WATER; DOCOSANOL; BUTYLOCTYL SALICYLATE; CAPRYLYL GLYCOL; CETEARYL OLIVATE; CETYL ALCOHOL; WATERMELON; ORANGE OIL, COLD PRESSED; GRAPEFRUIT; COCONUT OIL; DIISOPROPYL ADIPATE; DODECANE; ETHYLHEXYLGLYCERIN; EUCALYPTUS OIL; GLYCERIN; GLYCERYL LAURATE; HELIANTHUS ANNUUS FLOWERING TOP; LAURYL LACTATE; PEPPERMINT OIL; BASIL; RICE BRAN OIL; PANTHENOL; PENTYLENE GLYCOL; PHENOXYETHANOL; POLYESTER-8 (1400 MW, CYANODIPHENYLPROPENOYL CAPPED); POLYSORBATE 20; POTASSIUM CETYL PHOSPHATE; ROSEMARY; SODIUM HYDROXIDE; SORBITAN OLIVATE; TOCOPHEROL; XANTHAN GUM

MELAN SPF-30 Broad Spectrum Lotion

Active Ingredients

Avobenzone 3.00%

Homosalate 8.00%

Octisalate 5.00%

Purpose

Sunscreen

Uses

- Helps prevent sunburn.
- higher SPF gives more sunburn protection
- retains SPF after 80 minutes of swimming or sweating
- If used as directed with other sun protection measures (see Directions), decreases the risk of skin cancer and early skin aging caused by the sun

Warnings

For external use only

Do not use

- on damaged or broken skin.

When using this product

- keep out of eyes. Rinse with water to remove.

Stop use and ask a doctor if

- rash or irritation develops and lasts.

Keep out of reach of children.

If swallowed, get medical help or contact a Poison Control Center right away.

If pregnant or breast-feeding,

ask a health professional before use

Directions

- Apply liberally 15 minutes before sun exposure and as needed.
- Children under 6 months of age: ask a doctor.
- Reapply:
- after 80 minutes of swimming or sweating
- immediately after towel drying
- at least every 2 hours
- Sun Protection Measures. Spending time in the sun increases your risk of skin cancer and early skin aging. To decrease the risk, regularly use a sunscreen with broad spectrum SPF of 15 or higher and other sun protection measures including:
- Limit time in the sun, especially from 10 a.m. - 2 p.m.
- Wear long-sleeved shirts, pants, hats, and sunglasses.

Other Information

- Protect the product in this container from excessive heat and direct sun.

Inactive Ingredients

Aloe Barbadensis Leaf (Aloe Vera Gel) Juice, Ammonium Acryloyldimethyltaurate/VP Copolymer, Aqua (Deionized Water), Behenyl Alcohol Butyloctyl Salicylate, Caprylyl Glycol, Cetearyl Olivate, Cetyl Alcohol, Citrullus Lanatus (Watermelon) Extract, Citrus Aurantium Dulcis (Orange) Oil, Citrus Grandis (Grapefruit) Oil, Cocos Nucifera (Coconut) Oil, Diisopropyl Adipate, Dodecane, Ethylhexylglycerin, Eucalyptus Globulus Oil, Glycerin, Glyceryl Laurate, Glyceryl Undecylenate, Helianthus Annuus (Sunflower) Oil, 1-2 Hexanediol, Lauryl Lactate, Mentha Piperita (Peppermint) Oil, Ocimum Basilicum (Basil) Extract, Oryza Sativa (Rice) Bran Oil, dl-Panthenol, Pentylene Glycol, Phenoxyethanol, Polycrylene, Polysorbate-20, Potassium Cetyl Phosphate, Rosmarinus Officinalis (Rosemary) Extract, Sodium Hydroxide, Sorbitan Olivate, Tocopherol (Vitamin E), Xanthan Gum.

Questions?

1-888-676-3890